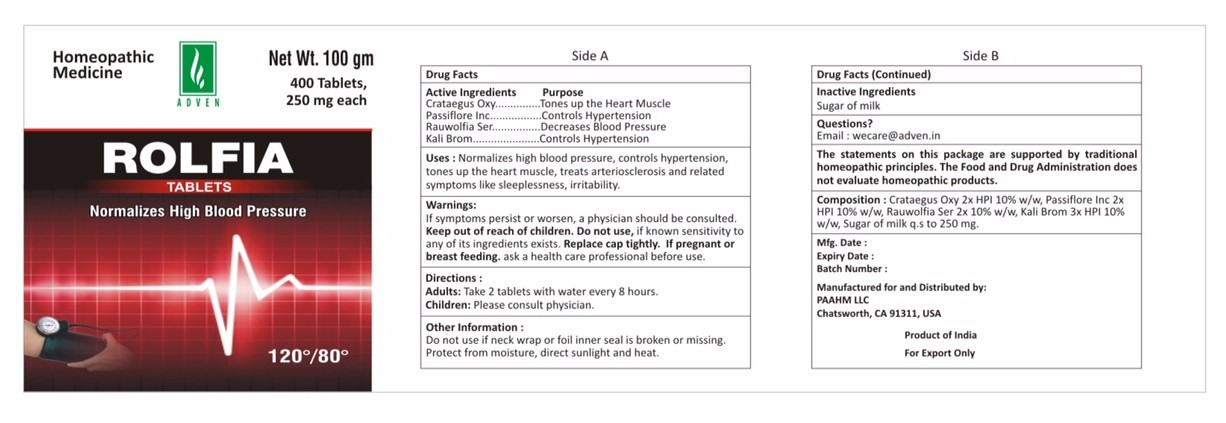 DRUG LABEL: rolfia
NDC: 69825-007 | Form: TABLET
Manufacturer: Adven Biotech Private Limited
Category: homeopathic | Type: HUMAN OTC DRUG LABEL
Date: 20160401

ACTIVE INGREDIENTS: POTASSIUM BROMIDE 3 [hp_X]/100 g; CRATAEGUS MONOGYNA LEAF 2 [hp_X]/100 g; PASSIFLORA INCARNATA ROOT 2 [hp_X]/100 g; RAUWOLFIA SERPENTINA 2 [hp_X]/100 g
INACTIVE INGREDIENTS: LACTOSE

Rolfia Tablets

ACTIVE INGREDIENT

Crataegus Oxyacantha, Passiflora Incarnata, Rauwolfia Serpentina, Kali Bromatum

DOSAGE AND ADMINISTRATION

Adults: Take 2 tablets with water every 8 hours.

Children under 18 years: Please consult physician.

Warnings:

If symptons persist or worsen, a physician should be consulted. Keep out of reach of children. Do not use, if known sentivity to any of its ingredients exists. Replace cap tightly. If pregnant or breast feeding, ask a health care professional before use.

PURPOSE

Tones up the Heart Muscle, Controls hypertension. Decrease Blood Pressure

Uses:

Normalizes high blood pressure, conrols hypertension, tones up the heart muscle, treats arteriosclerosis and related symptoms like sleeplessness, irritability.

INACTIVE INGREDIENT

Sugar of milk

Do not use if neck wrap or foil inner seal is broken or missing. Protect from moisture, direct sunlight and heat.